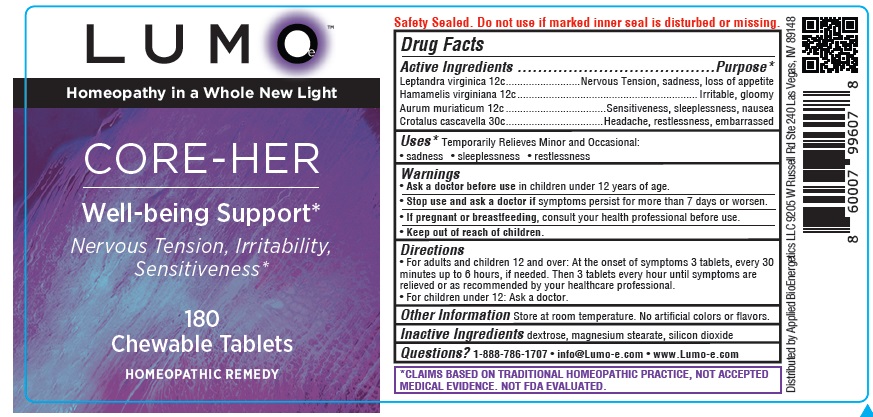 DRUG LABEL: LUMOe CORE-HER Well-being Support
NDC: 81425-006 | Form: TABLET, CHEWABLE
Manufacturer: Applied Bioenergetics, LLC
Category: homeopathic | Type: HUMAN OTC DRUG LABEL
Date: 20251110

ACTIVE INGREDIENTS: VERONICASTRUM VIRGINICUM ROOT 12 [hp_C]/1 1; HAMAMELIS VIRGINIANA ROOT BARK/STEM BARK 12 [hp_C]/1 1; GOLD TRICHLORIDE 12 [hp_C]/1 1; CROTALUS DURISSUS TERRIFICUS VENOM 30 [hp_C]/1 1
INACTIVE INGREDIENTS: DEXTROSE; MAGNESIUM STEARATE; SILICON DIOXIDE

LUMOe CORE-HER Well-being Support

Drug Facts

Active Ingredients
Leptandra virginica 12c
Hamamelis virginiana 12c
Aurum muriaticum 12c
Crotalus cascavella 30c

Purpose*
Leptandra virginica ..........................Nervous Tension, sadness, loss of appetite
Hamamelis virginiana ............................................................... Irritable, gloomy
Aurum muriaticum ...................................Sensitiveness, sleeplessness, nausea
Crotalus cascavella ................................Headache, restlessness, embarrassed

INDICATIONS AND USAGE

Uses* Temporarily Relieves Minor and Occasional:
• sadness • sleeplessness • restlessness

Warnings
• Ask a doctor before use in children under 12 years of age.
• Stop use and ask a doctor if symptoms persist for more than 7 days or worsen.
• If pregnant or breastfeeding, consult your health professional before use.

• Keep out of reach of children.

Directions
• For adults and children 12 and over: At the onset of symptoms 3 tablets, every 30
minutes up to 6 hours, if needed. Then 3 tablets every hour until symptoms are
relieved or as recommended by your healthcare professional.
• For children under 12: Ask a doctor.

Other Information Store at room temperature. No artificial colors or flavors.

Inactive Ingredients dextrose, magnesium stearate, silicon dioxide

QUESTIONS

Questions? 1-888-786-1707 • info@Lumo-e.com • www.Lumo-e.com

*CLAIMS BASED ON TRADITIONAL HOMEOPATHIC PRACTICE, NOT ACCEPTED
MEDICAL EVIDENCE. NOT FDA EVALUATED.

LUMOe CORE-HER Well-being Support Labeling

LUMOe
Homeopathy in a Whole New Light

CORE-HER
Well-being Support*
Nervous Tension, Irritability,
Sensitiveness*

180
Chewable Tablets
HOMEOPATHIC REMEDY

Distributed by Applied BioEnergetics LLC 9205 W Russell Rd Ste 240 Las Vegas, NV 89148

res